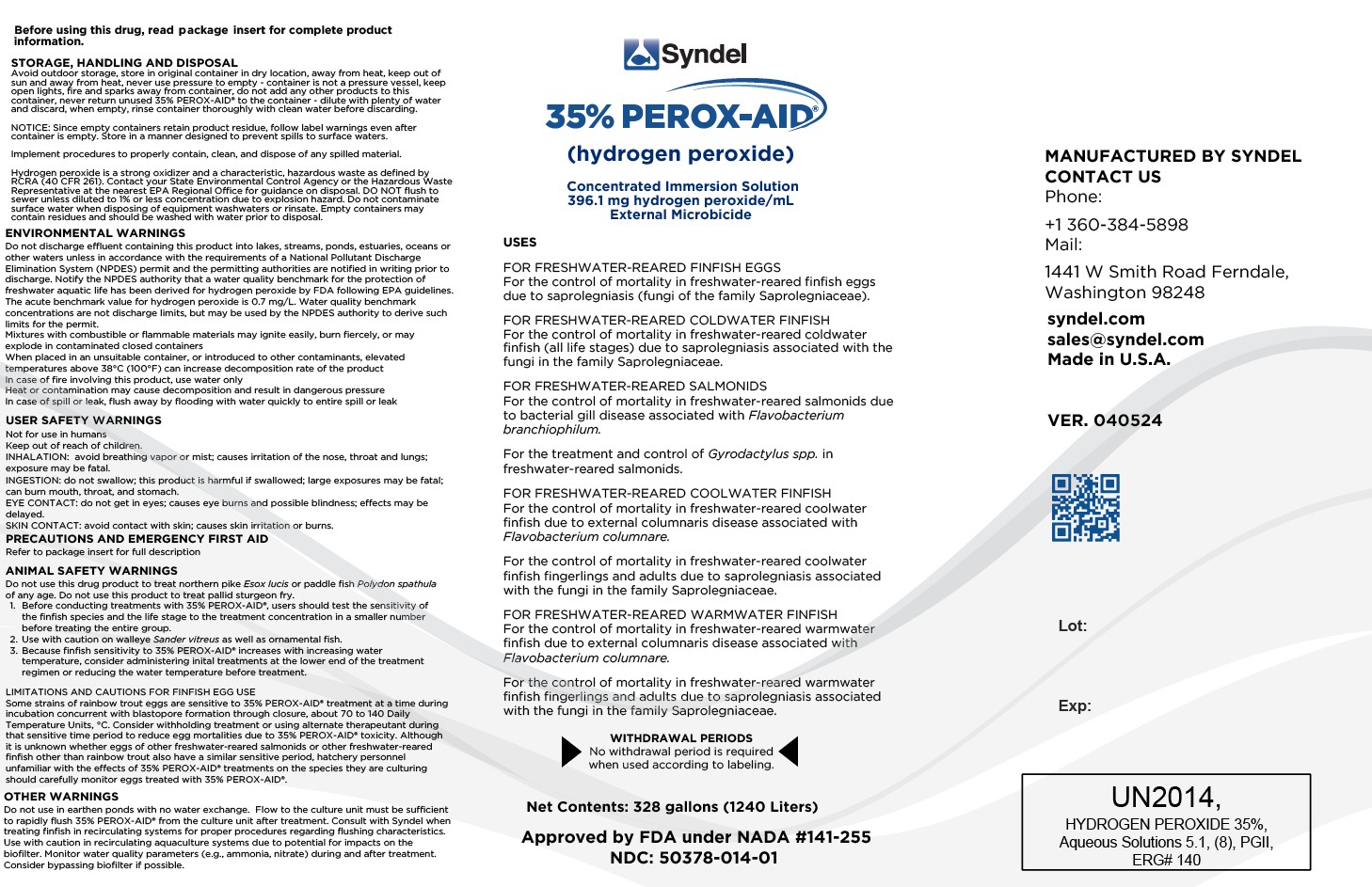 DRUG LABEL: 35% Perox-Aid
NDC: 50378-014 | Form: SOLUTION
Manufacturer: Western Chemical Inc.
Category: animal | Type: OTC ANIMAL DRUG LABEL
Date: 20250305

ACTIVE INGREDIENTS: HYDROGEN PEROXIDE 350 g/1 L
INACTIVE INGREDIENTS: Water

35% PeroxAid (hydrogen peroxide)
Concentrated Immersion Solution
396.1 mg hydrogen peroxide/mL
External microbicide
Active Drug Ingredient
hydrogen peroxide

USES
FOR FRESHWATER-REARED FINFISH EGGS
For the control of mortality in freshwater-reared finfish eggs due to saprolegniasis (fungi of the family Saprolegniaceae).
FOR FRESHWATER-REARED COLDWATER FINFISH
For the control of mortality in freshwater-reared coldwater finfish (all life stages) due to saprolegniasis associated with the fungi in the family Saprolegniaceae.
FOR FRESHWATER-REARED SALMONIDS
For the control of mortality in freshwater-reared salmonids due to bacterial gill disease associated with Flavobacterium branchiophilum.
For the treatment and control of Gyrodactylus spp. in freshwater-reared salmonids.

FOR FRESHWATER-REARED COOLWATER FINFISH
For the control of mortality in freshwater-reared coolwater finfish due to external columnaris disease associated with Flavobacterium
columnare.
For the control of mortality in freshwater-reared coolwater finfish fingerlings and adults due to saprolegniasis associated with the fungi in the family Saprolegniaceae.
FOR FRESHWATER-REARED WARMWATER FINFISH
For the control of mortality in freshwater-reared warmwater finfish due to external columnaris disease associated with Flavobacterium columnare.
For the control of mortality in freshwater-reared warmwater finfish fingerlings and adults due to saprolegniasis associated with the fungi in the family Saprolegniaceae.

DESCRIPTION
35% PEROX-AID® (hydrogen peroxide) is a concentrated immersion solution containing 396.1 mg hydrogen peroxide per mL.

Hydrogen Peroxide (H2O2) …………………………………….. 35% (W/W)

Water and inert ingredients ……………………………………. 65% (W/W)

WITHDRAWAL PERIODS
No withdrawal period is required when used according to labeling.

USER SAFETY WARNINGS
Not for use in humans. Keep out of reach of children.
INHALATION (Breathing):

Avoid breathing vapor or mist; causes irritation of the nose, throat and lungs; exposure may be fatal.

INGESTION (Swallowing):

Do not swallow; this product is harmful if swallowed; large exposures may be fatal; can burn mouth, throat, and stomach.

EYE CONTACT:

Do not get in eyes; causes eye burns and possible blindness; effects may be delayed.

SKIN CONTACT:

Avoid contact with skin; causes skin irritation or burns.

HUMAN PRECAUTIONS

 Wear chemical safety goggles.
 Wear neoprene, butyl, or vinyl gloves.
 Keep out of reach of children.
 Use only in adequate ventilation.
 Keep containers tightly closed when not in use.
 Wear suitable protective clothing.

EMERGENCY FIRST AID

In case of contact, immediately flush eyes or skin with plenty of water for at least 15 minutes. Call a physician.

 Remove and wash contaminated clothing and shoes promptly and thoroughly.
 If inhaled, move to fresh air. If not breathing, give artificial respiration. If breathing is difficult, give oxygen. Call a physician.
 If swallowed, do not induce vomiting. Give large quantities of water. Never give anything by mouth to an unconscious person. Call a physician.
 Bring the package insert with you to the health care professional.

ENVIRONMENTAL WARNINGS
Do not discharge effluent containing this product into lakes, streams, ponds, estuaries, oceans or other waters unless in accordance with the require-ments of a National Pollutant Discharge Elimination System (NPDES) permit and the permitting authorities are notified in writing prior to discharge. Notify the NPDES authority that a water quality benchmark for the protection of freshwater aquatic life has been derived for hydrogen peroxide by FDA following EPA guidelines. The acute benchmark value for hydrogen peroxide is 0.7 mg/L. Water quality benchmark concentrations are not discharge limits, but may be used by the NPDES authority to derive such limits for the permit. Additional environmental information on hydrogen peroxide and the benchmark value are available in an environmental assessment available at https://animaldrugsatfda.fda.gov/adafda/app/search/public/document/down-loadEA/123.

Mixtures with combustible or flammable materials may ignite easily, burn fiercely, or may explode in contaminated closed containers.
When placed in an unsuitable container, or introduced to other contaminants, elevated temperatures above 38oC (100oF) can increase the decomposition rate of the product.

 In case of fire involving this product, use water only.
 Heat or contamination may cause decomposition and result in dangerous pressure

In case of spill or leak, flush away by flooding with water applied quickly to entire spill or leak

DIRECTIONS

1. Dissolve 35% PEROX-AID® in culture water before addition to the culture unit to achieve required dose based on active ingredient. Consider using aeration to help disperse the chemical and to ensure adequate oxygenation levels.
2. Before treatment, remove dead eggs or finfish and clean rearing units to be treated.

The formula to determine the correct volume of 35% PEROX-AID® required for treatment is:

Treatment conc. mg/L (as H2O2)____ X treatment vol. (L) x 1,000 mL/L = ml of 35% PEROX-AID®

396,100 mg H2O2 / L 35% PEROX-AID®

1. FRESHWATER-REARED FINFISH EGGS
Apply 35% PEROX-AID® at the full concentration in the table below in continuous flow water supply of finfish egg incubation units for 15 minutes. Treat finfish egg incubation units once per day on consecutive or alternate days until hatch to control mortalities associated with external saprolegniasis in a tiered dosing system as follows:

USE | SPECIES/CLASS | DOSE (AS H2O2) | DURATION (per day)
For the control of mortality due to saprolegniasis associated with fungi in the family Saprolegniaceae | All cold and coolwater freshwater-reared finfish eggs^1 | 500-1,000 mg/L | 15 minutes
 |  | 750-1,000 mg/L | 15 minutes

1 An initial bioassay on a small number is recommended before treating the entire group. The amount of 35% PEROX-AID® required for treatment is dependent on the volume of water treated (which equals the water flow rate times 15 min; 10 L/min x 15 = 150L).
Example calculation:
500 mg/L (as H2O2) X 150L x 1,000 mL/L = 189 mL 35% PEROX-AID® 396,100 mg H2O2 /L 35% PEROX-AID®

2. FRESHWATER-REARED FINFISH
Apply 35% PEROX-AID® at the full concentration in the table (milligrams hydrogen peroxide per liter of culture water [mg/L; equivalent to parts per million (ppm)]) in continuous flow water supply or as a static bath in finfish culture units once per day on alternate days for three treatments.

USE | SPECIES CLASS | DOSE (AS H2O2) | DURATION PER DAY
For the control of mortality due to saprolegniasis associated with fungi in the family Saprolegniaceae | In freshwater-reared coldwater finfish including salmonids (all life stages) | 75 mg/L | 60 minutes
 | In freshwater-reared coolwater finfish fingerling and adults
 | In freshwater-reared warmwater finfish fingerling and adults
For the control of mortality due to bacterial gill disease associated with Flavobacterium branchiophilum | In freshwater-reared salmonids | 100 mg/L; or 50-100 mg/L | 30 minutes; or 60 minutes
For the treatment and control of Gyrodactylus spp | In freshwater-reared salmonids | 100 mg/L; 50 mg/L | 30 minutes; or 60 minutes
For the control of mortality due to external columnaris disease associated with Flavobacterium columnare | In freshwater-reared coolwater and warmwater finfish fingerling and adults; In freshwater-reared coolwater finfish fry and warmwater finfish fry | 50 mg/L | 60 minutes

HOW SUPPLIED

35% PEROX-AID® is available as: 5-gallon container (19L), 55-gallon drum (208L), and 328-gallon container (1240L).

STORAGE, HANDLING

 Avoid outdoor storage.
 Store in original container in dry location.
 Keep out of sun and away from heat.
 Never use pressure to empty – container is not a pressure vessel.
 Keep open lights, fire, and sparks away from container.
 Do not add any other products to this container.
 Never return unused 35% PEROX-AID® to the container – dilute with plenty of water and discard.
 When empty, rinse container thoroughly with clean water before discarding.

NOTICE: Since empty containers retain product residue, follow label warnings even after container is empty.
Store in a manner designed to prevent spills to surface waters. Implement procedures to properly contain, clean, and dispose of any spilled material.
Hydrogen peroxide is a strong oxidizer and a characteristic, hazardous waste as defined by RCRA (40 CFR 261). Contact your State Environmental Control Agency or the Hazardous Waste Representative at the nearest EPA Regional Office for guidance on disposal.
DO NOT flush to sewer unless diluted to 1% or less concentration due to explosion hazard. Do not contaminate surface water when disposing of equipment washwaters or rinsate. Empty containers may contain residues and should be washed with water prior to disposal.

QUESTIONS/COMMENTS

For Chemical Emergency, Spill, Leak, Fire, Exposure or Accident, CALL CHEMTREC, DAY OR NIGHT 1-800-424-9300.
To report side effects or for technical assistance, or to obtain a copy of the SDS, contact Syndel at 1-800-283-5292 or www.syndel.com. For additional information about reporting side effects for animal drugs, contact FDA at 1-888-FDA-VETS or online at http://www.fda.gov/reportanimalae.